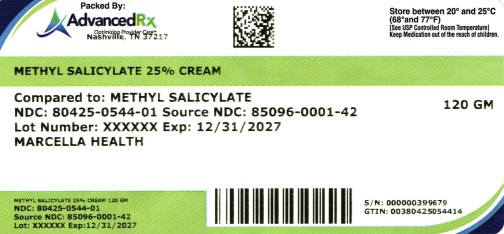 DRUG LABEL: Methyl Salicylate 25% Cream
NDC: 80425-0544 | Form: CREAM
Manufacturer: Advanced Rx of Tennessee, LLC
Category: otc | Type: HUMAN OTC DRUG LABEL
Date: 20250808

ACTIVE INGREDIENTS: METHYL SALICYLATE 250 mg/1 g
INACTIVE INGREDIENTS: XANTHAN GUM; MINERAL OIL; PEPPERMINT OIL; WHITE PETROLATUM; ALOE BARBADENSIS LEAF; GLYCERYL STEARATE SE; CETYL ALCOHOL; PROPYLENE GLYCOL; PEG-100 STEARATE; WATER; PHENOXYETHANOL

Methyl Salicylate 25% Cream

Active ingredient

Methyl Salicylate 25%

Purpose

External analgesic

Uses

For the temporary relief of minor aches and pains of muscles and joints, such as simple backache, lumbago, arthritis, neuralgia, strains, bruises, and sprains.

Warnings

For external use only.

When using this product

- Avoid contact with the eyes
- Do not use in larger quantities, particularly over raw surfaces or blistered areas
- Do not apply to wounds or damaged skin
- Do not bandage

Stop use and ask a doctor if

- allergic reaction occurs
- condition worsens or does not improve within 7 days
- symptoms clear up and return within a few days
- redness, irritation, swelling, pain or other symptoms begin or increase

Keep out of the reach of children.

If swallowed, get medical help or contact a Poison Control Center right away

Directions

adults and children 2 years and older | apply externally to the affected area up to 3 to 4 times a day
children under 2 years | ask a doctor

Other Information

- May be applied under occlusive dressing.
- Store at 20-25-C (68-77°F); excursions permitted to 15-30°C (59-86°F). See USP Controlled Room Temperature.

Inactive Ingredients

Aloe barbadensis leaf extract, cetyl alcohol, glyceryl stearate SE, mineral oil, PEG-100 stearate, peppermint oil, phenoxyethanol, propylene glycol, purified water, stearyl alcohol, white petrolatum, xanthan gum.

MANUFACTURED FOR:
Marcella Health

Cheyene, WY 82001
Questions or Comments
(307) 410-3813 or info@marcellahealth.com